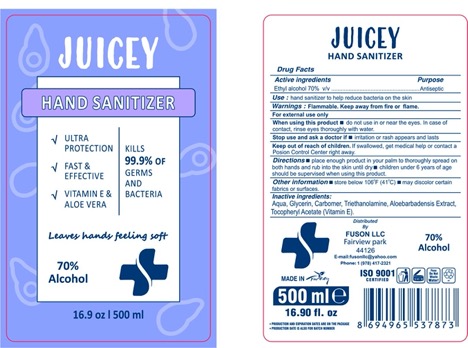 DRUG LABEL: Juicey Hand Sanitizer
NDC: 78141-900 | Form: GEL
Manufacturer: Fuson LLC
Category: otc | Type: HUMAN OTC DRUG LABEL
Date: 20200609

ACTIVE INGREDIENTS: ALCOHOL 70 mL/100 mL
INACTIVE INGREDIENTS: WATER 30 mL/100 mL; CARBOMER 980 0.25 g/100 mL; TROLAMINE 0.15 mL/100 mL; GLYCERIN 1 mL/100 mL; ALOE VERA LEAF 0.01 g/100 mL; .ALPHA.-TOCOPHEROL ACETATE, D- 0.01 g/100 mL

JUICEY HAND SANITIZER- FUSON LLC

Active Ingredient(s)

Ethyl Alcohol 70% v/v. Purpose: Antiseptic

Purpose

Antiseptic, Hand Sanitizer

Use

Hand Sanitizer to help reduce bacteria that potentially can cause disease. For use when soap and water are not available.

Warnings

For external use only. Flammable. Keep away from heat or flame

Do not use

- in children less than 2 months of age
- on open skin wounds

When using this product keep out of eyes, ears, and mouth. In case of contact with eyes, rinse eyes thoroughly with water.
Stop use and ask a doctor if irritation or rash occurs. These may be signs of a serious condition.
Keep out of reach of children. If swallowed, get medical help or contact a Poison Control Center right away.

Stop use and ask a doctor if irritation or rash occurs. These may be signs of a serious condition.

Keep out of reach of children. If swallowed, get medical help or contact a Poison Control Center right away.

Directions

- Place enough product on hands to cover all surfaces. Rub hands together until dry.
- Supervise children under 6 years of age when using this product to avoid swallowing.

Other information

- Store between 15-30C (59-86F)
- Avoid freezing and excessive heat above 40C (104F)

Inactive ingredients

Water, Glycerin, Carbomer, Triethanolamine, Aloebarbadensis Extract, Tocopheryl Acetate

Package Label - Principal Display Panel

100 ml NDC: 78141-900-01

250 ml NDC: 78141-900-02

500 ml NDC: 78141-900-03

1000 ml NDC: 78141-900-04

3780 ml NDC: 78141-900-05